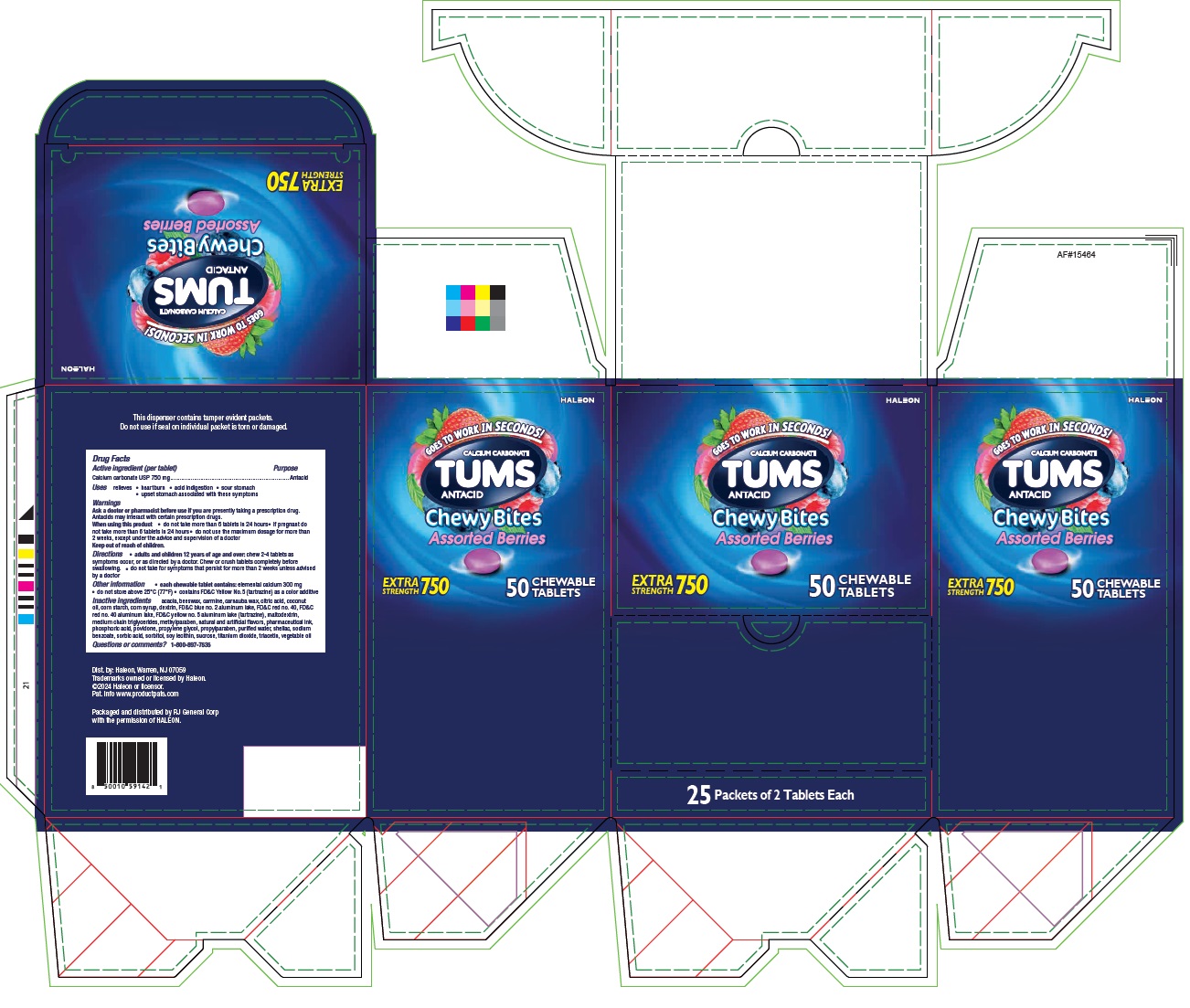 DRUG LABEL: Tums Antacid Chewy Bites
NDC: 70264-046 | Form: TABLET
Manufacturer: R J General Corporation
Category: otc | Type: HUMAN OTC DRUG LABEL
Date: 20251117

ACTIVE INGREDIENTS: CALCIUM CARBONATE 750 mg/1 1
INACTIVE INGREDIENTS: ACACIA; BEESWAX; CARMINIC ACID; CARNAUBA WAX; CITRIC ACID; COCONUT OIL; STARCH, CORN; CORN SYRUP; FD&C BLUE NO. 2 ALUMINUM LAKE; FD&C RED NO. 40; FD&C RED NO. 40 ALUMINUM LAKE; FD&C YELLOW NO. 5 ALUMINUM LAKE; MALTODEXTRIN; ICODEXTRIN; MEDIUM-CHAIN TRIGLYCERIDES; METHYLPARABEN; ALCOHOL; PHOSPHORIC ACID; POVIDONE; PROPYLENE GLYCOL; PROPYLPARABEN; WATER; SHELLAC; SODIUM BENZOATE; SORBIC ACID; SORBITOL; SOYBEAN LECITHIN; SUCROSE; TITANIUM DIOXIDE; TRIACETIN; CORN OIL

CALCIUM CARBONATE Tums Antacid Chewy Bites

Drug Facts

Active ingredients (in each tablet) | Purpose
Calcium Carbonate USP 750mg | Antacid

Uses
relieves

- heartburn
- acid indigestion
- sour stomach
- upset stomach associated with these symptoms

Warnings

Ask a doctor or pharmacist before use if you arepresently taking a prescription drug. Antacids may interact with certain prescription drugs.

When using this product

- do not take more than 6 tablets in 24 hours
- if pregnant do not take more than 6 tablets in 24 hours
- do not use the maximum dosage for more than 2 weeks except under the advice and supervision of a doctor

Keep out of reach of children.

Directions

- adults and children 12 years of age and over:chew 2-4 tablets as symptoms occur, or as directed by a doctor
- do not take for symptoms that persist for more than 2 weeks unless advised by a doctor

Other information

- each chewable tablet contains:elemental calcium 300mg
- do not store above 25°C (77°F)
- contains FD&C Yellow No.5 (tartrazine) as a color additive

Inactive ingredients

acacia, beeswax, carmine, carnauba wax, citric acid, coconut oil, corn starch, corn syrup, dextrin, FD&C blue no. 2 aluminum lake, FD&C red no. 40, FD&C red no. 40 aluminum lake, FD&C yellow no. 5 aluminum lake (tartrazine),maltodextrin, medium chain triglycerides,methylparaben, natural and artificial flavors, pharmaceutical ink, phosphoric acid, povidone, propylene glycol, propylparaben, purified water, shellac, sodium benzoate, sorbic acid, sorbitol, soy lecithin, sucrose, titanium dioxide, triacetin, vegetable oil

Questions or comments?
1-800-897-7535

Dist. by:

Haleon,Warren, NJ 07059

Packaged and distributed by RJ Corp with the permission of HALEON

PRINCIPAL DISPLAY PANEL

Calcium Carbonate Tums Antacid Chewy Bites Assorted Berries - NDC 70264-046-01 - 50 Chewable Tablets Carton Label